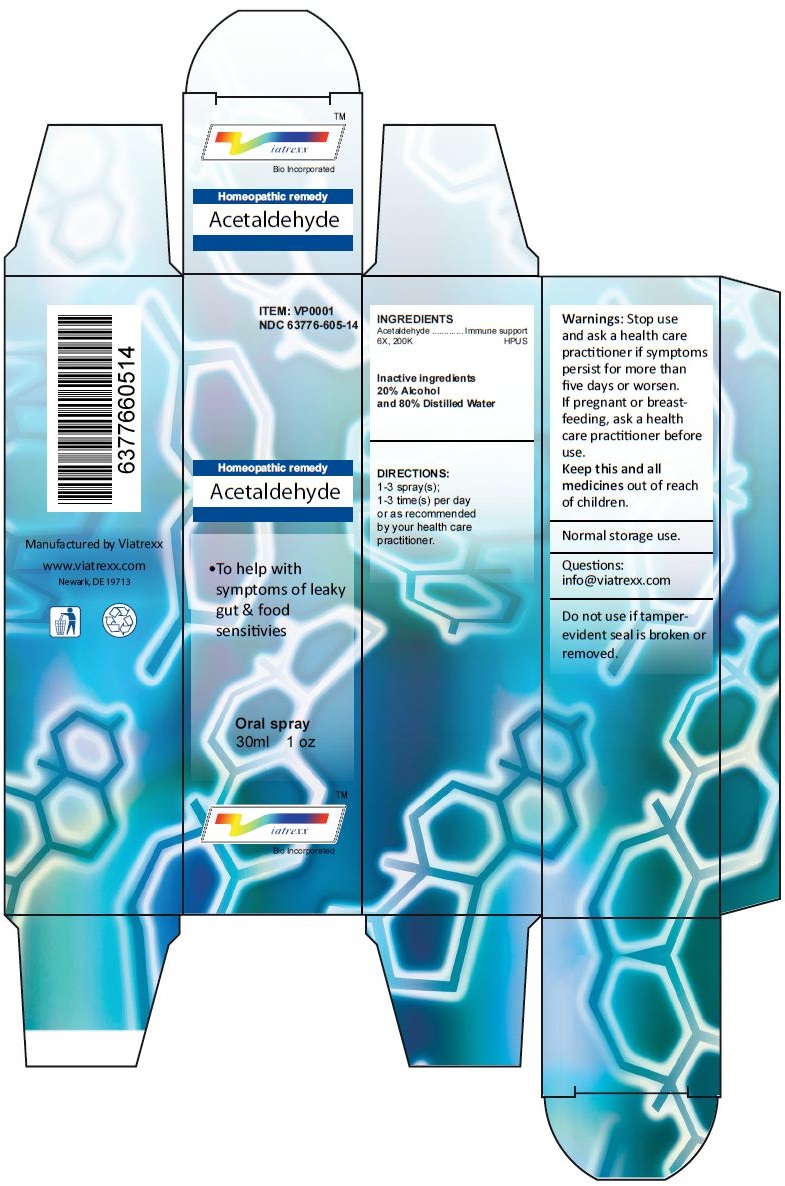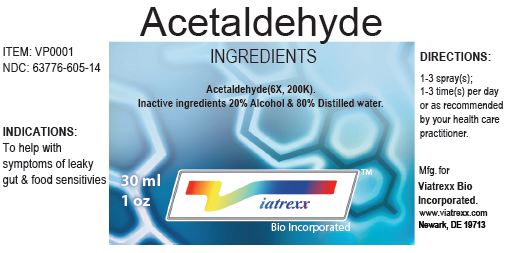 DRUG LABEL: Acetaldehyde 
NDC: 63776-605 | Form: SPRAY
Manufacturer: VIATREXX BIO INCORPORATED
Category: homeopathic | Type: HUMAN OTC DRUG LABEL
Date: 20120724

ACTIVE INGREDIENTS: Acetaldehyde 200 {kp_C}/1 mL
INACTIVE INGREDIENTS: Alcohol; Water

Acetaldehyde

Active Ingredients

Acetaldehyde 6X, 200K

Purpose:

Acetaldehyde | Immune support

Uses

To help with symptoms of leaky gut & food sensitivies

Warnings

Stop use and ask a health care practitioner if symptoms persist for more than five days or worsen. If pregnant or breastfeeding, ask a health care practitioner before use.

Dosage

1-3 spray(s); 1-3 time(s) per day or as recommended by your health care practitioner.

KEEP OUT OF REACH OF CHILDREN

Keep this and all medicines out of reach of children.

Other Ingredients

20% Alcohol and 80% Distilled Water.

Other Information

Normal storage use.
Do not use if tamper-evident seal is broken or removed.

Questions

info@viatrexx.com

Principal Display Panel

ITEM: VP0001
NDC 63776-605-14
Homeopathic remedy
Acetaldehyde
• To help with symptoms of leaky gut & food sensitivies
Oral spray
30ml 1 oz
Viatrexx™ Bio Incorporated
Manufactured by Viatrexx
www.viatrexx.com
Newark, DE 19713

Acetaldehyde
30 ml
1 oz
Viatrexx™ Bio Incorporated
ITEM: VP0001
NDC: 63776-605-14
INDICATIONS:
To help with symptoms of leaky gut & food sensitivies
DIRECTIONS:
1-3 spray(s); 1-3 time(s) per day or as recommended by your health care practitioner.
Mfg. for
Viatrexx Bio Incorporated.
www.viatrexx.com
Newark, DE 19713